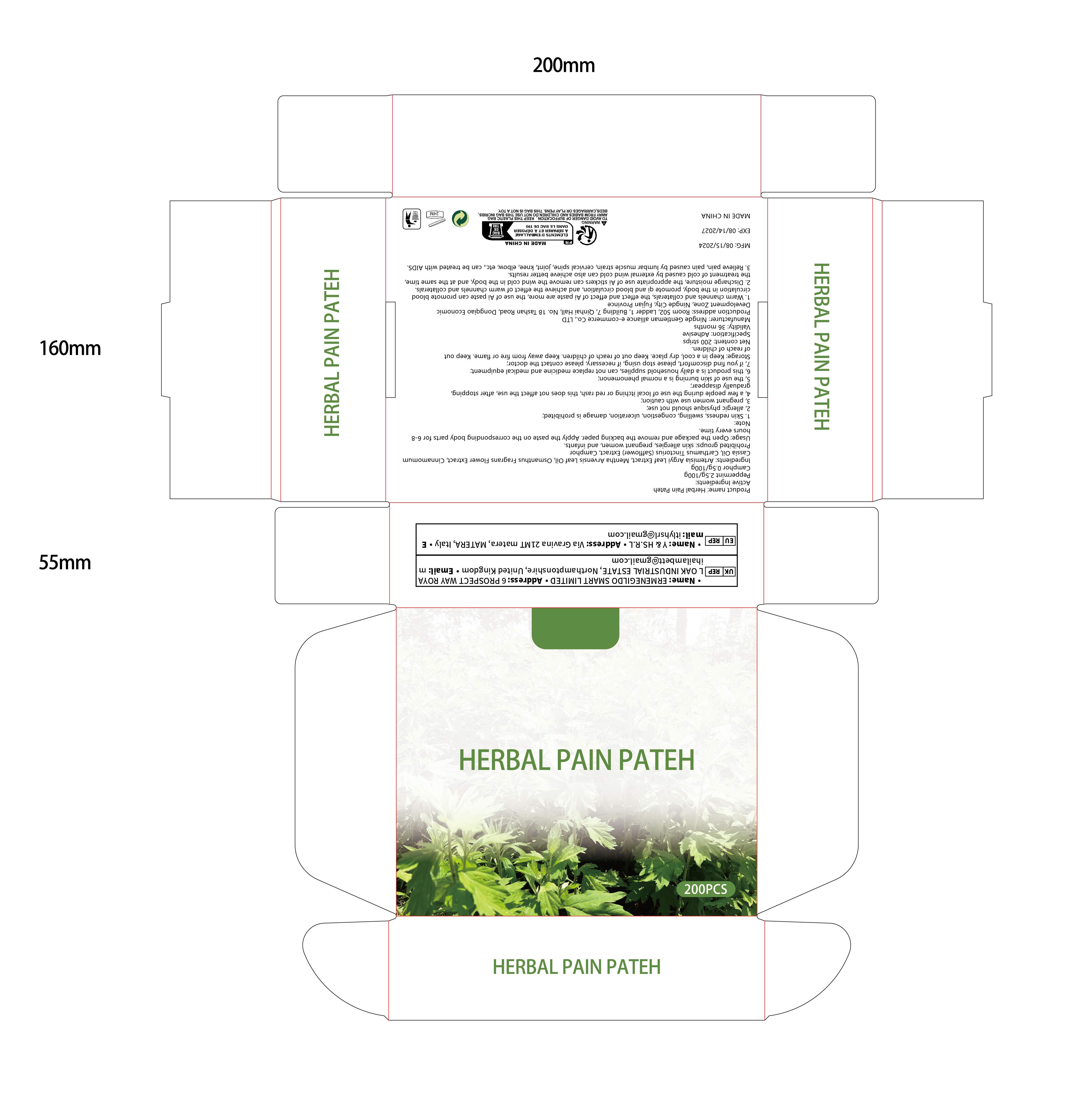 DRUG LABEL: Herbal Pain Pateh
NDC: 84667-001 | Form: PATCH
Manufacturer: Ningde Gentleman alliance e-commerce Co., LTD
Category: otc | Type: HUMAN OTC DRUG LABEL
Date: 20240731

ACTIVE INGREDIENTS: PEPPERMINT 2.5 g/8 h; CAMPHOR (NATURAL) 0.5 g/8 h
INACTIVE INGREDIENTS: OSMANTHUS FRAGRANS FLOWER; ARTEMISIA ARGYI LEAF; CHINESE CINNAMON OIL; MENTHA ARVENSIS LEAF OIL; SAFFLOWER

ACTIVE

Peppermint 2.5g/100g

Camphor 0.59/100g

INACTIVE

Ingredients: Artemisia Argyi Leaf Extract, Mentha Arvensis Leaf Oil, Osmanthus Fragrans flower Extract, CinnamomumCassia Oil, Carthamus Tinctorius (Safflower) Extract,

PURPOSE

1. Warm channels and collaterals, the effect and effect of Ai paste are more, the use of Ai paste can promote bloodcirculation in the body, promote gi and blood circulation, and achieve the effect of warm channels and collaterals.

2. Discharge moisture, the appropriate use of Ai stickers can remove the wind cold in the body, and at the same timethe treatment of cold caused by external wind cold can also achieve better results.

3. Relieve pain, pain caused by lumbar muscle strain, cervical spine, joint, knee, elbow, etc, can be treated with AlDS

Warning

1.Skin redness,swelling, congestion, ulceration, damage is prohibited;2,allergic physique should not use;

3,pregnant women use with caution;

4, a few people during the use of local itching or red rash, this does not affect the use, after stopping

gradually disappear;

5,the use of skin burning is a normal phenomenon;

6, this product is a daily householdsupplies, can not replace medicine and medical equipment,

7, if you find discomfort, please stop using, if necessary, please contact the doctor;Storage: Keep in a cool, dry place. Keep out of reach of children. Keep away from fire or flame. Keep outof reach of children.Net content: 200 strips

Do not use

Prohibited groups: skin allergies, pregnant women, and infants.

stop use

1.Skin redness,swelling, congestion, ulceration, damage is prohibited;2,allergic physique should not use;

3,pregnant women use with caution;

4, a few people during the use of local itching or red rash, this does not affect the use, after stopping gradually disappear;

When use

1. Warm channels and collaterals, the effect and effect of Ai paste are more, the use of Ai paste can promote bloodcirculation in the body, promote gi and blood circulation, and achieve the effect of warm channels and collaterals.

2. Discharge moisture, the appropriate use of Ai stickers can remove the wind cold in the body, and at the same timethe treatment of cold caused by external wind cold can also achieve better results.

3. Relieve pain, pain caused by lumbar muscle strain, cervical spine, joint, knee, elbow, etc, can be treated with AlDS

OUT OF CHILDREN

if you find discomfort, please stop using, if necessary, please contact the doctor;Storage: Keep in a cool, dry place. Keep out of reach of children. Keep away from fire or flame. Keep outof reach of children

HOW TO USE

Open the package and remove the backing paper. Apply the paste on the corresponding body parts for 6-8hours every time.

Dosage

Specification: Adhesive

Apply the paste on the corresponding body parts for 6-8hours every time.